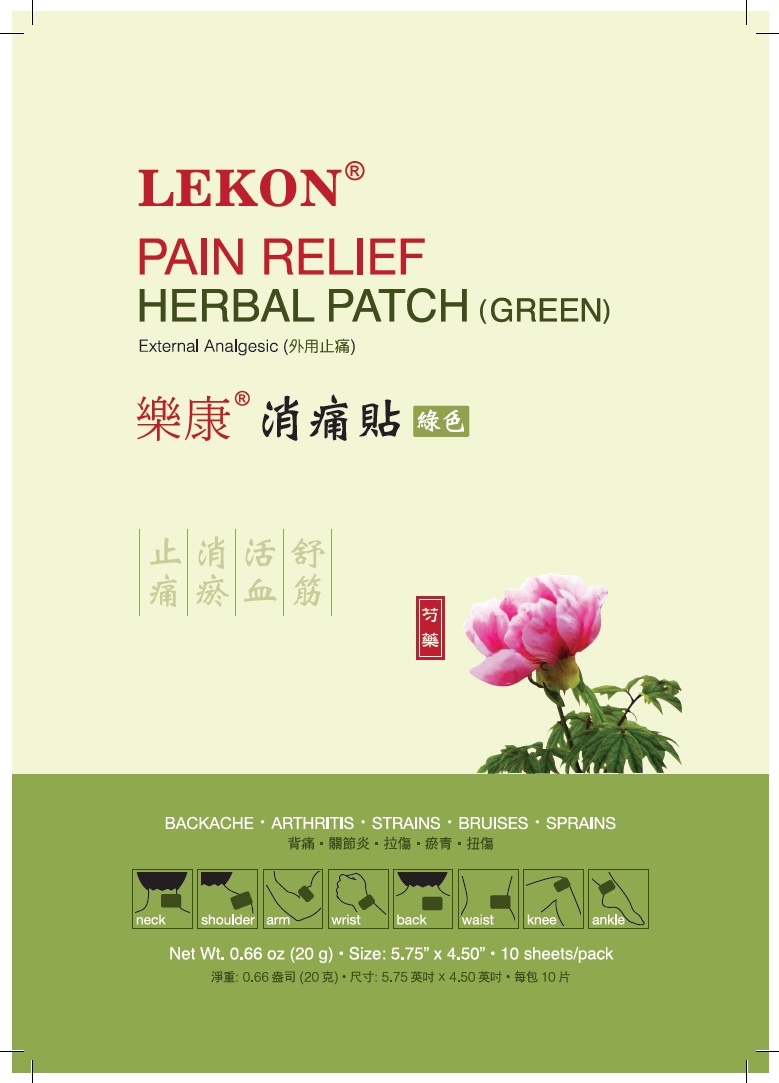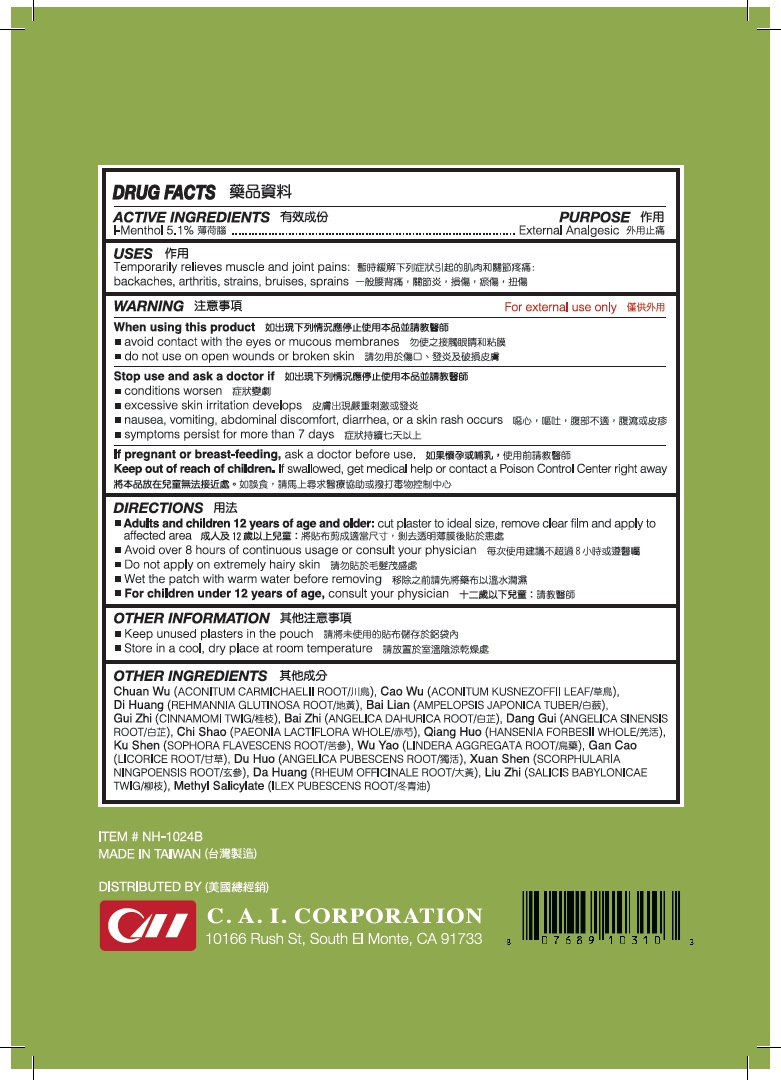 DRUG LABEL: LK Herbal Patch
NDC: 85954-002 | Form: PATCH
Manufacturer: CAI Industries Corp.
Category: otc | Type: HUMAN OTC DRUG LABEL
Date: 20250821

ACTIVE INGREDIENTS: LEVOMENTHOL 5.1 g/1 1
INACTIVE INGREDIENTS: ACONITUM CARMICHAELII ROOT; ACONITUM KUSNEZOFFII LEAF; REHMANNIA GLUTINOSA ROOT; AMPELOPSIS JAPONICA TUBER; ANGELICA DAHURICA ROOT; ANGELICA SINENSIS ROOT; PAEONIA LACTIFLORA WHOLE; HANSENIA FORBESII WHOLE; LINDERA AGGREGATA ROOT; LICORICE; ANGELICA PUBESCENS ROOT; SCROPHULARIA NINGPOENSIS ROOT; RHEUM OFFICINALE ROOT; SOLIDAGO VIRGAUREA FLOWERING TOP; METHYL SALICYLATE

Active Ingredients

Menthol 5.1%

Purpose

External analgesic

Uses

Temporarily relieves muscle and joint pains: backaches, arthritis, strains, bruises, sprains

Warnings

For external use only

When using this product

- avoid contact with the eyes or mucous membranes
- do not use on wounds or broken skin

Stop use and ask a doctor if

- conditions worsen
- excessive skin irritation develops
- nausea, vomiting, abdominal discomfort, diarrhea, or a skin rash occurs
- symptoms persists for more than 7 days

If pregnant or breast-feeding, ask a doctor before use.

Keep out of reach of children. If swallowed, get medical help or contact a Poison Control Center right away.

Directions

- Adults and children 12 years of age and older: cut plaster to ideal size, remove clear film and apply to affected area
- Avoid over 8 hours of continuous usage or consult your physician
- Do not apply on extermely hairy skin
- Wet the patch with warm water before removing
- Children under 12 years of age: consult your physician

Other Information

- Keep unused plasters in the pouch
- Store in a cool dry place at room temperature.

Inactive ingredients

Chuan Wu ACONITUM CARMICHAELII ROOT, Cao Wu (ACONITUM KUSNEZOFFII LEAF), Di Huang - Radix Rehmanniae, Bai Lian AMPELOPSIS JAPONICA TUBER, Bai Zhi - ANGELICA DAHURICA ROOT, Dang Gui (ANGELICA SINENSIS ROOT), Chi Shao whole PAEONIA LACTIFLORA WHOLE, Qiang Huo whole (HANSENIA FORBESII WHOLE, Wu Yao - LINDERA AGGREGATA ROOT, Gan Cao (LICORICE), Du Huo (ANGELICA PUBESCENS ROOT), Xuan Shen (SCROPHULARIA NINGPOENSIS ROOT), Da Huang (RHEUM OFFICINALE ROOT), Liu Zhi (SOLIDAGO VIRGAUREA FLOWERING TOP, Methyl salicylate